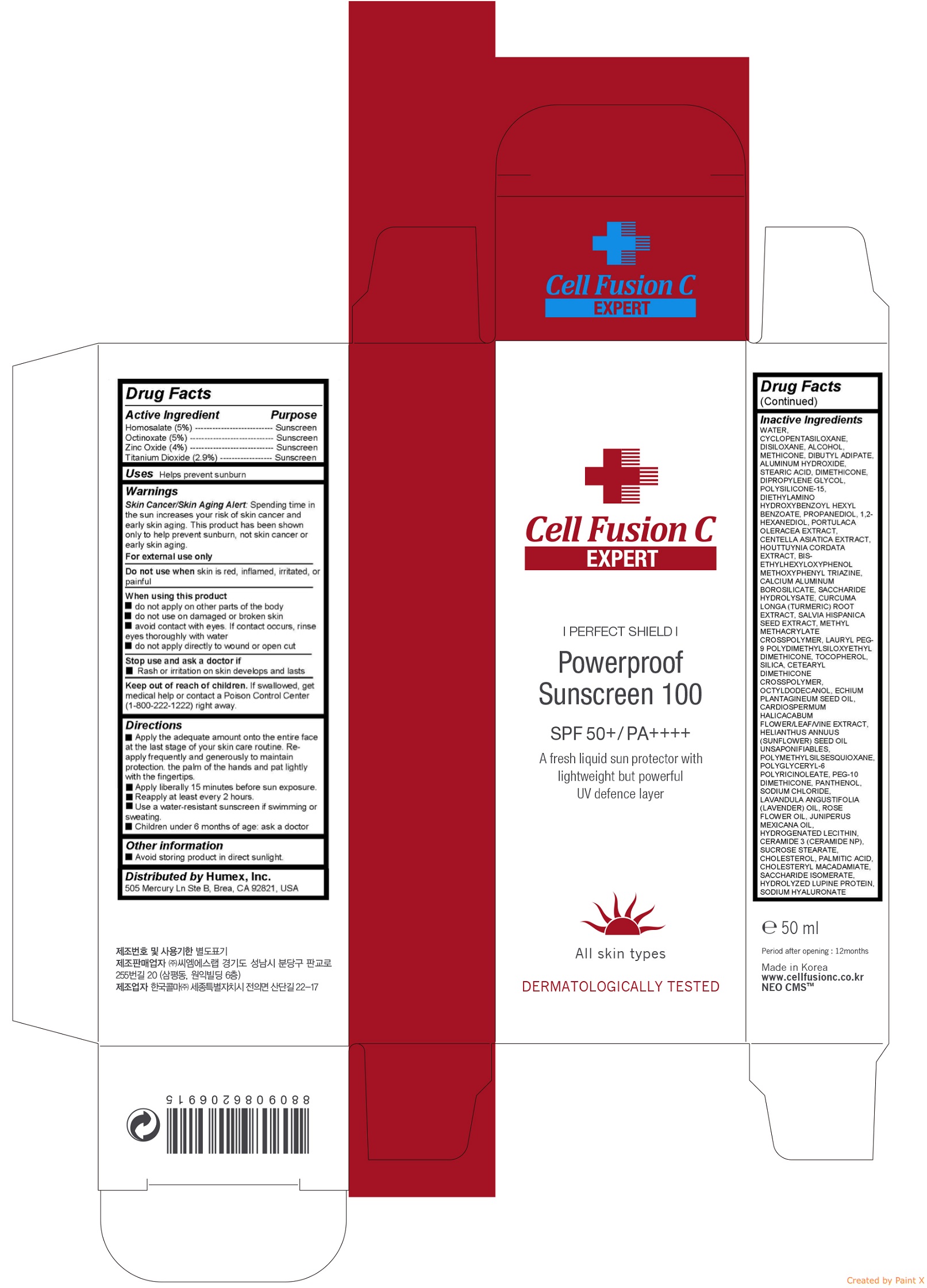 DRUG LABEL: Powerproof Sunscreen 100
NDC: 52554-1112 | Form: CREAM
Manufacturer: CMS LAB Inc.
Category: otc | Type: HUMAN OTC DRUG LABEL
Date: 20171106

ACTIVE INGREDIENTS: Homosalate 2.5 g/50 mL; Octinoxate 2.5 1/50 mL; Zinc Oxide 2 g/50 mL; Titanium Dioxide 1.45 g/50 mL
INACTIVE INGREDIENTS: WATER; CYCLOMETHICONE 5; HEXAMETHYLDISILOXANE; ALCOHOL; METHICONE (20 CST); DIBUTYL ADIPATE; ALUMINUM HYDROXIDE; STEARIC ACID; DIMETHICONE; DIPROPYLENE GLYCOL; POLYSILICONE-15; DIETHYLAMINO HYDROXYBENZOYL HEXYL BENZOATE; PROPANEDIOL; 1,2-HEXANEDIOL; PURSLANE; CENTELLA ASIATICA; HOUTTUYNIA CORDATA FLOWERING TOP; BEMOTRIZINOL; CALCIUM ALUMINUM BOROSILICATE; INVERT SUGAR; TURMERIC; CHIA SEED

Powerproof Sunscreen 100

Active ingredients

Homosalate (5%)

Octinoxate (5%)

Zinc Oxide (4%)

Titanium Dioxide (2.52%)

Purpose

Sunscreen

Uses

Helps prevent sunburn

Warnings

Skin Cancer/Skin Aging Alert: Spending time in the sun increases your risk of skin cancer and early skin aging. This product has been shown only to help prevent sunburn, not skin cancer or early skin aging.

For external use only

Do not use when skin is red, inflamed, irritated, or painful

When using this product do not apply on other parts of the body do not use on damaged or broken skin avoid contact with eyes. If contact occurs, rinse eyes thoroughly with water do not apply directly to wound or open cut

Stop use and ask a doctor if Rash or irritation on skin develops and lasts

Keep out of reach of children

If swallowed, get medical help or contact a Poison Control Center (1-800-222-1222) right away.

Directions

- Apply the adequate amount onto the entire face at the last stage of your skin care routine. Re-apply frequently and generously to maintain protection. the palm of the hands and pat lightly with the fingertips.

- Apply liberally 15 minutes before sun exposure.

- Reapply at least every 2 hours.

- Use a water-resistant sunscreen if swimming or sweating.

- Children under 6 months of age: ask a doctor

Inactive ingredients

WATER, CYCLOPENTASILOXANE, DISILOXANE, ALCOHOL, METHICONE, DIBUTYL ADIPATE, ALUMINUM HYDROXIDE, STEARIC ACID, DIMETHICONE, DIPROPYLENE GLYCOL, POLYSILICONE-15, DIETHYLAMINO HYDROXYBENZOYL HEXYL BENZOATE, PROPANEDIOL, 1,2-HEXANEDIOL, PORTULACA OLERACEA EXTRACT, CENTELLA ASIATICA EXTRACT, HOUTTUYNIA CORDATA EXTRACT, BIS-ETHYLHEXYLOXYPHENOL METHOXYPHENYL TRIAZINE, CALCIUM ALUMINUM BOROSILICATE, SACCHARIDE HYDROLYSATE, CURCUMA LONGA (TURMERIC) ROOT EXTRACT, SALVIA HISPANICA SEED EXTRACT, METHYL METHACRYLATE CROSSPOLYMER, LAURYL PEG-9 POLYDIMETHYLSILOXYETHYL DIMETHICONE, TOCOPHEROL, SILICA, CETEARYL DIMETHICONE CROSSPOLYMER, OCTYLDODECANOL, ECHIUM PLANTAGINEUM SEED OIL, CARDIOSPERMUM HALICACABUM FLOWER/LEAF/VINE EXTRACT, HELIANTHUS ANNUUS (SUNFLOWER) SEED OIL UNSAPONIFIABLES, POLYMETHYLSILSESQUIOXANE, POLYGLYCERYL-6 POLYRICINOLEATE, PEG-10 DIMETHICONE, PANTHENOL, SODIUM CHLORIDE, LAVANDULA ANGUSTIFOLIA (LAVENDER) OIL, ROSE FLOWER OIL, JUNIPERUS MEXICANA OIL, HYDROGENATED LECITHIN, CERAMIDE 3 (CERAMIDE NP), SUCROSE STEARATE, CHOLESTEROL, PALMITIC ACID, CHOLESTERYL MACADAMIATE, SACCHARIDE ISOMERATE, HYDROLYZED LUPINE PROTEIN, SODIUM HYALURONATE